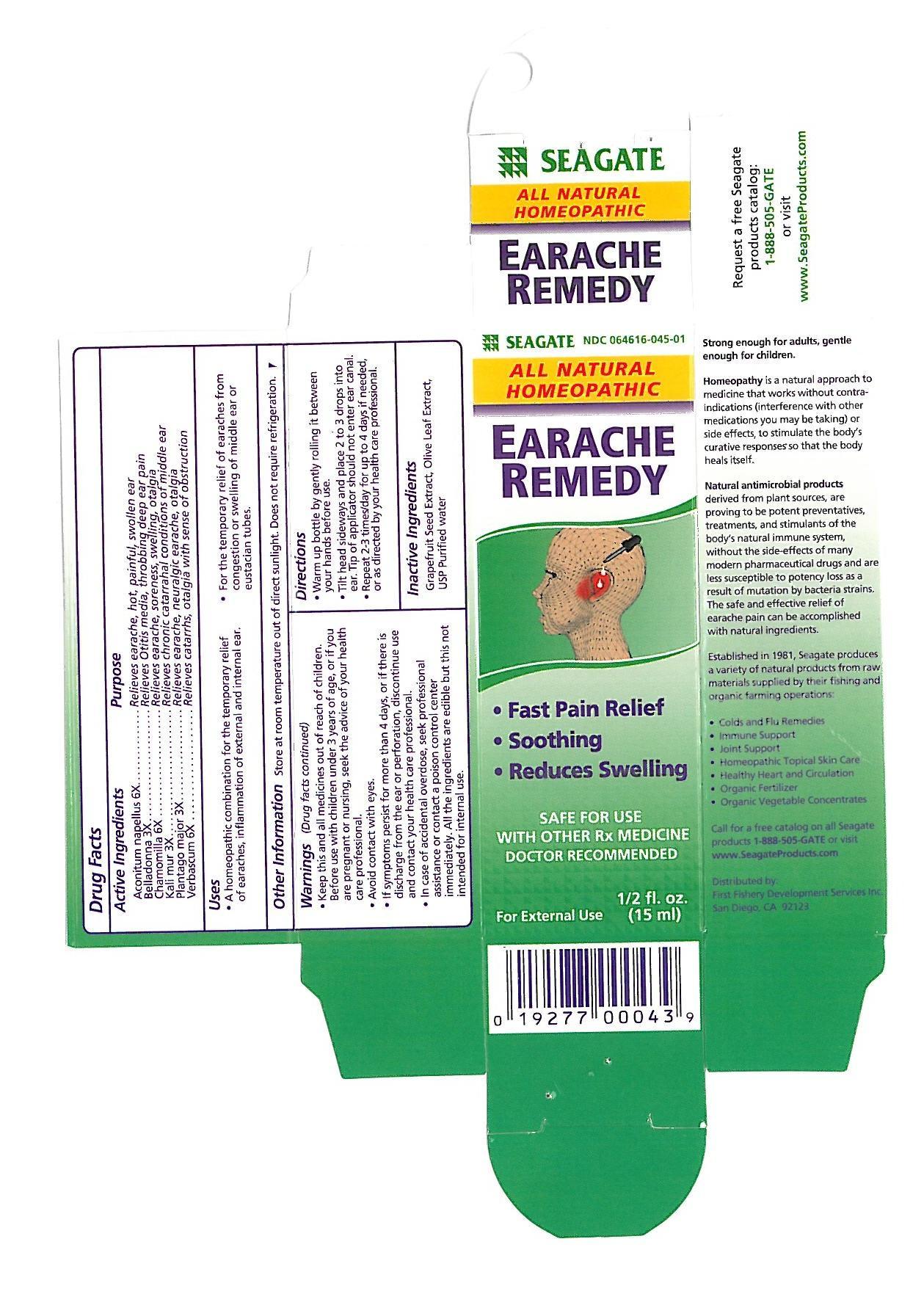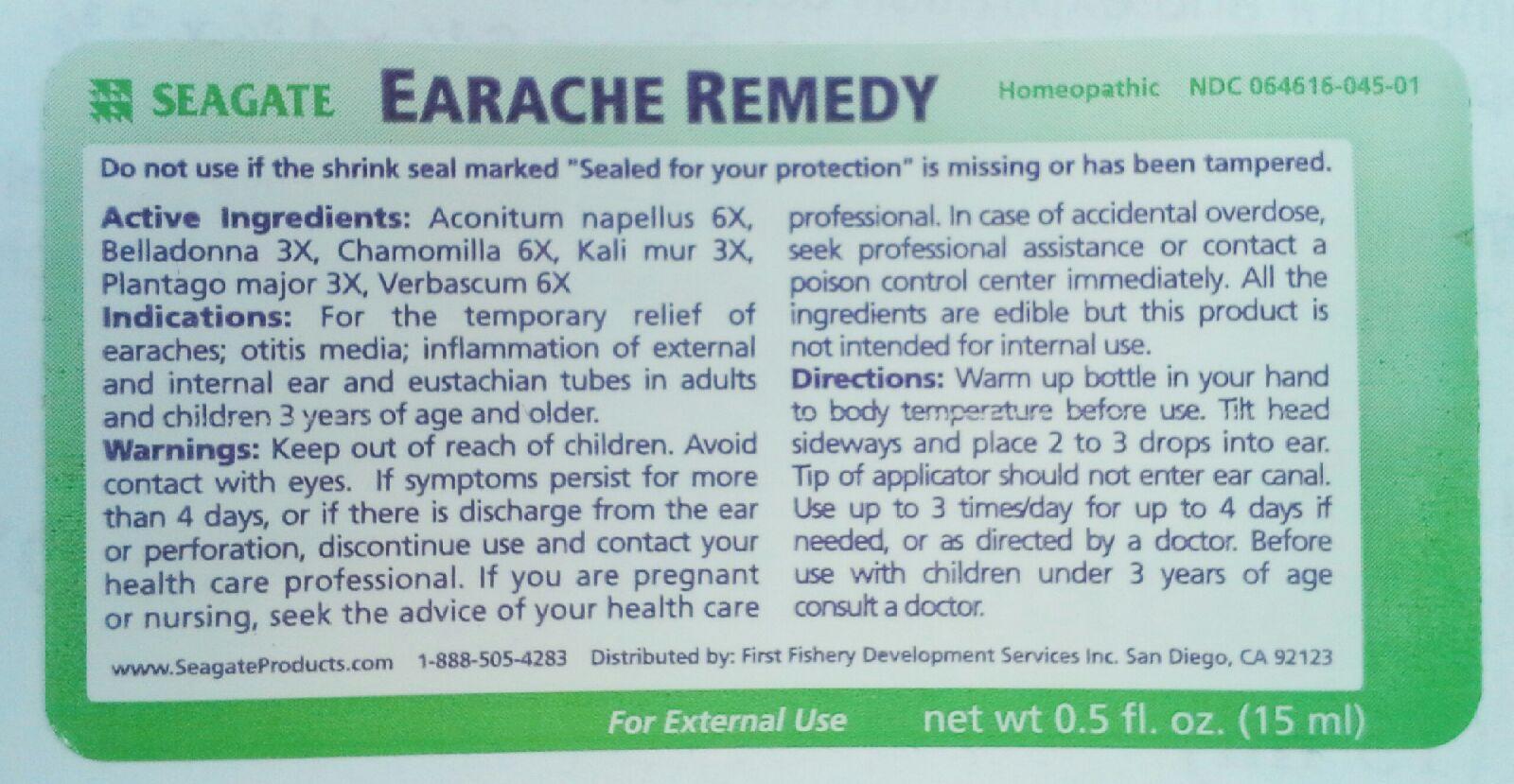 DRUG LABEL: Earache Remedy
NDC: 64616-045 | Form: LIQUID
Manufacturer: Vitality Works, Inc.
Category: homeopathic | Type: HUMAN OTC DRUG LABEL
Date: 20251217

ACTIVE INGREDIENTS: ACONITUM NAPELLUS 6 [hp_X]/1 mL; ATROPA BELLADONNA 3 [hp_X]/1 mL; POTASSIUM CHLORIDE 3 [hp_X]/1 mL; PLANTAGO MAJOR 3 [hp_X]/1 mL; MATRICARIA RECUTITA 6 [hp_X]/1 mL; VERBASCUM THAPSUS 6 [hp_X]/1 mL
INACTIVE INGREDIENTS: BENZALKONIUM CHLORIDE; OLEA EUROPAEA LEAF; WATER; COBALT DISODIUM EDETATE

Earache Remedy

Earache Remedy

Aconitum napellus 6X

Belladonna 3X

Chamomilla 6X

Kali mur 3X

Plantago major 3X

Verbascum 6X

Earache Remedy

Grapefruit Seed Extract, Olive Leaf Extract, USP Purified Water

Earache Remedy

Keep this and all medicines out of reach of children. Before use with children under 3 years of age, or if you are pregnant or nursing seek the advice of your health care professional. Avoid contact with eyes. If symptoms persist for more than 4 days, or if there is discharge from the ear or perforation, discontinue use and contact your health care professional. In case of accedental overdose, seek professional assistance or contact a poison control center immediately. All the ingredients are edible but this is not intended for internal use.

Earache Remedy

Keep this and all medicines out of reach of children.

Earache Remedy

A homeopathic combination for the temporary relief or earaches, inflammation of the external and internal ear. For the temporary relief of earches from congestion or swelling of middle ear or eustacian tubes.

DOSAGE AND ADMINISTRATION

Warm up bottle by gently rolling it between your hands before use. Tilt head sideways and place 2 to 3 drops into ear. Tip of applicator should not enter ear canal. Repeat 2-3 times/day for up to 4 days, if needed, or as directed by your health care professional.

Earache Remedy

Aconitum napellus - relieves earache, hot, painful, swollen ear.

Belladonna - relieves Otitis media, throbbing deep ear pain.

Chamomilla - relieves eache, soreness, swelling, otalgia.

Kali mur - relieves chronic catarrahal conditions of middle ear.

Plantago major - relieves earache, neuralgic earache, otalgia.

Verbascum - relieves catarrhs, otalgia with sense of obstruction.